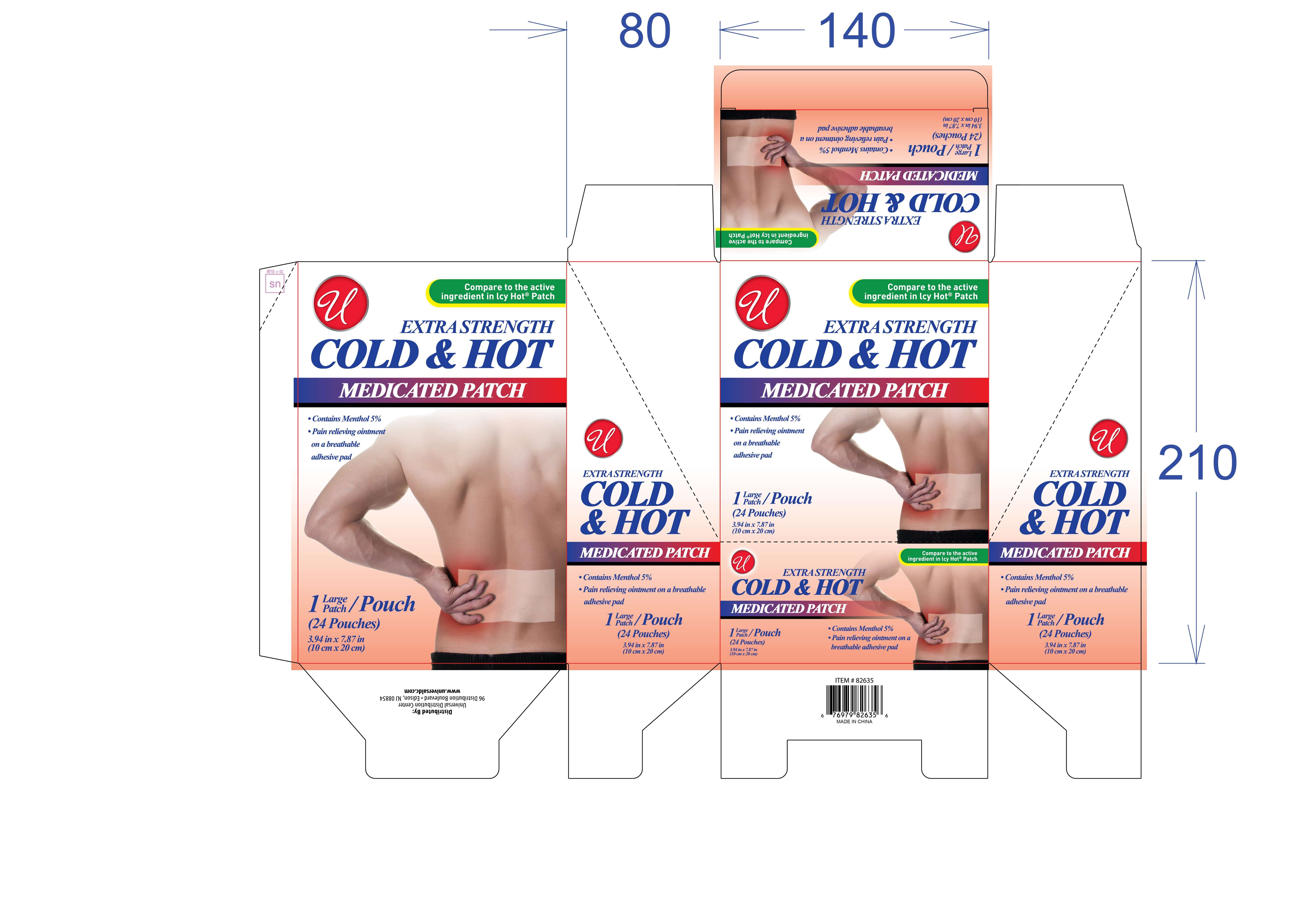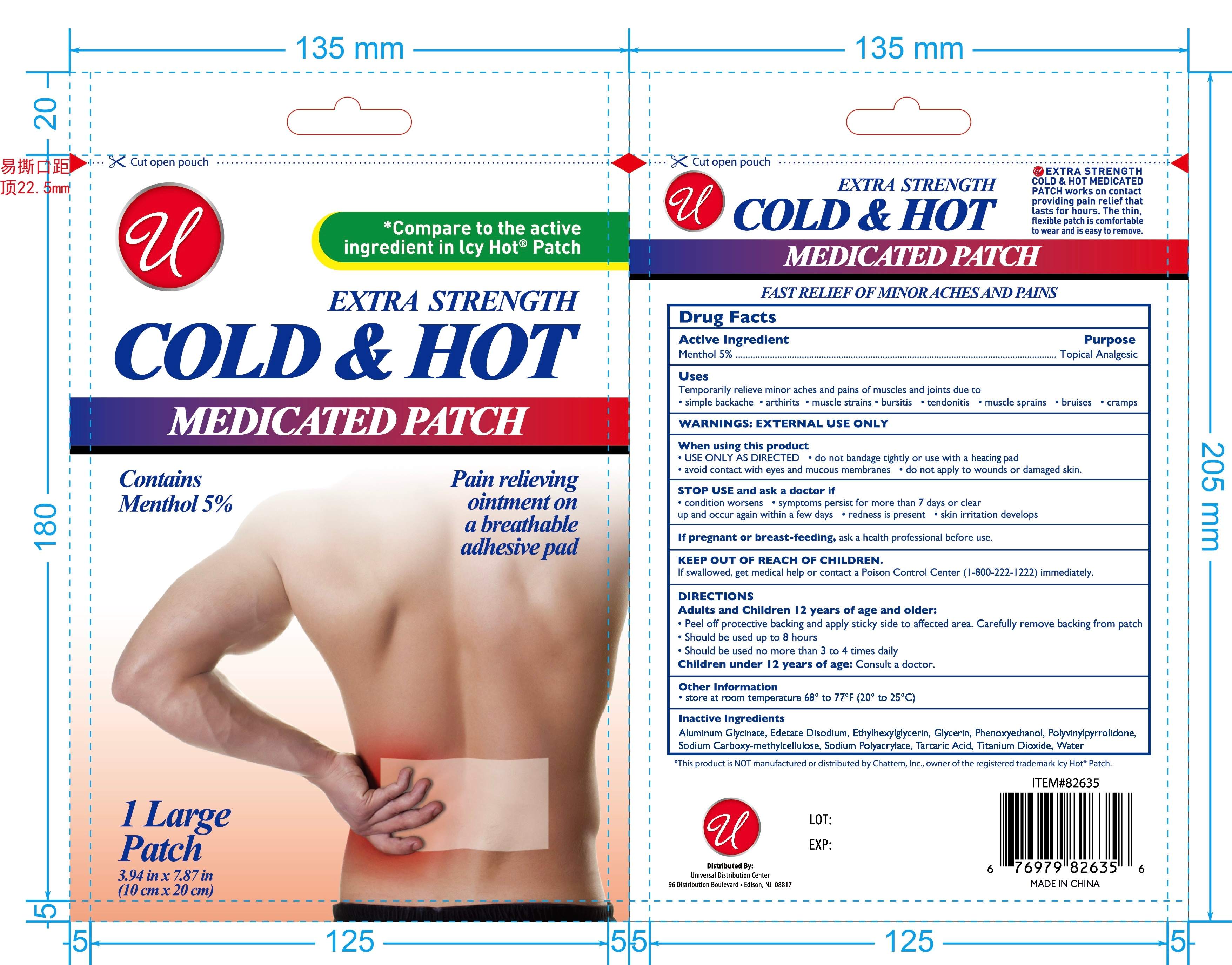 DRUG LABEL: COLD AND HOT MEDICATED Patch
NDC: 83559-015 | Form: PATCH
Manufacturer: Henan Enokon Medical Instrument Co., Ltd.
Category: otc | Type: HUMAN OTC DRUG LABEL
Date: 20260131

ACTIVE INGREDIENTS: MENTHOL 5 g/100 1
INACTIVE INGREDIENTS: ETHYLHEXYLGLYCERIN; CARBOXYMETHYLCELLULOSE SODIUM, UNSPECIFIED; GLYCERIN; TARTARIC ACID; DIHYDROXYALUMINUM AMINOACETATE ANHYDROUS; WATER; EDETATE DISODIUM; PHENOXYETHANOL; SODIUM POLYACRYLATE (2500000 MW); POVIDONE, UNSPECIFIED; TITANIUM DIOXIDE

83559-015

Active Ingredient

Menthol 5%

Purpose

Topical Analgesic

Use

Temporarily relieve minor aches and pains of muscles and joints due to
• simple backache • arthritis • muscle strains • bursitis • tendonitis • muscle sprains • bruises • cramps

Warnings

EXTERNAL USE ONLY

When Using

• USE ONLY AS DIRECTED • do not bandage tightly or use with a heating pad
• avoid contact with eyes and mucous membranes • do not apply to wounds or damaged skin.

Stop Use

• condition worsens • symptoms persist for more than 7 days or clear up and occur again within a few days • redness is present • skin irritation develops

Ask Doctor

If pregnant or breast-feeding, ask a health professional before use.

Keep Out Of Reach Of Children

If swallowed, get medical help or contact a Poison Control Center (1-800-222-1222) immediately.

Directions

Adults and Children 12 years of age and older:
• Peel off protective backing and apply sticky side to affected area. Carefully remove backing from patch
• Should be used up to 8 hours
• Should be used no more than 3 to 4 times daily
Children under 12 years of age: Consult a doctor.

Other information

• store at room temperature 68° to 77°F (20° to 25°C)

*Compare to the active ingredient in Icy Hot® Patch

EXTRA STRENGTH

Contains Menthol 5%

Pain relieving ointment on a breathable adhesive pad

EXTRA STRENGTH COLD & HOT MEDICATED PATCH works on contact providing pain relief that lasts for hours. The thin, flexible patch is comfortable to wear and is easy to remove.

FAST RELIEF OF MINOR ACHES AND PAINS

*This product is NOT manufactured or distributed by Chattem Inc., owner of the registered trademark Icy Hot® Patch.

Distributed By:
Universal Distribution Center
96 Distribution Boulevard • Edison, NJ 08817

MADE IN CHINA

www.universaldc.com

Inactive ingredients

Aluminum Glycinate, Edetate Disodium, Ethylhexylglycerin, Glycerin, Phenoxyethanol, Polyvinylpyrrolidone, Sodium Carboxy-methylcellulose, Sodium Polyacrylate, Tartaric Acid, Titanium Dioxide, Water

Questions

www.universaldc.com